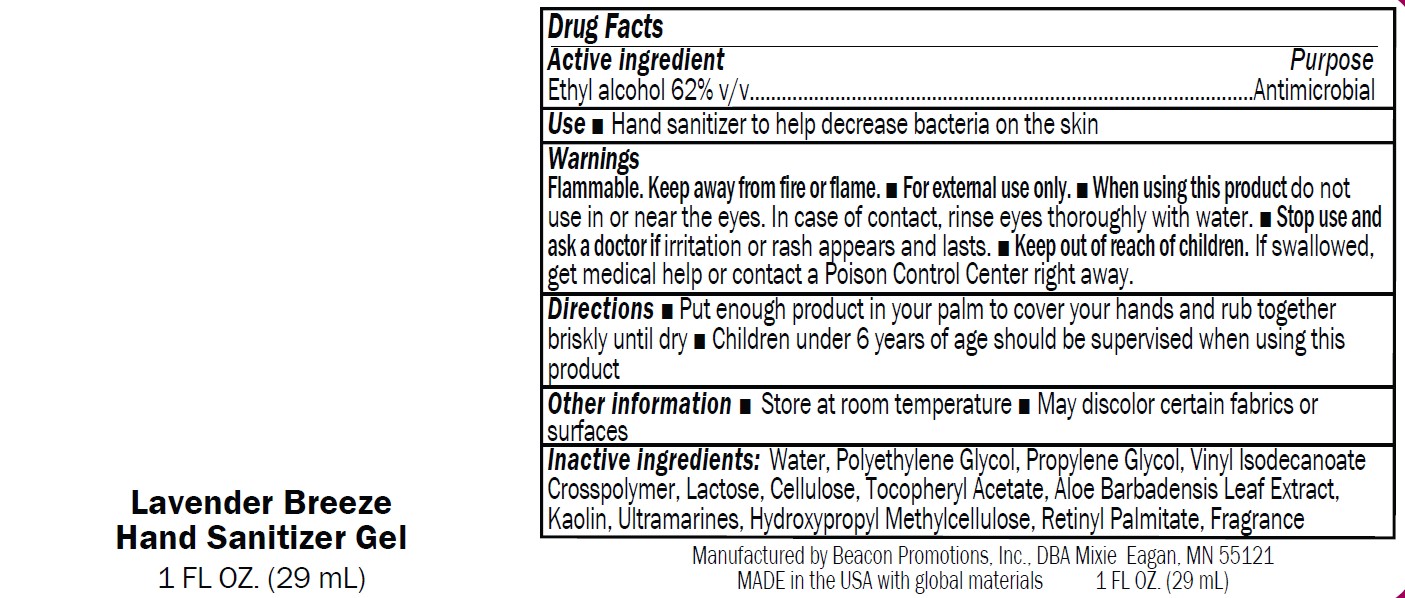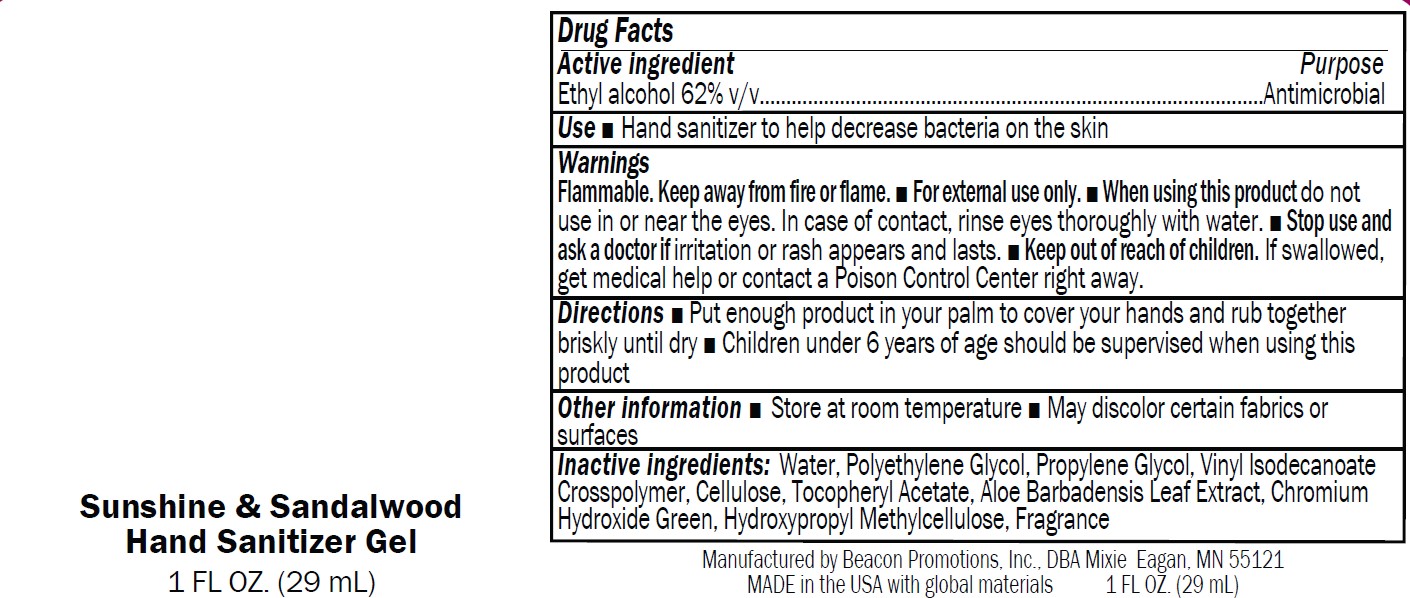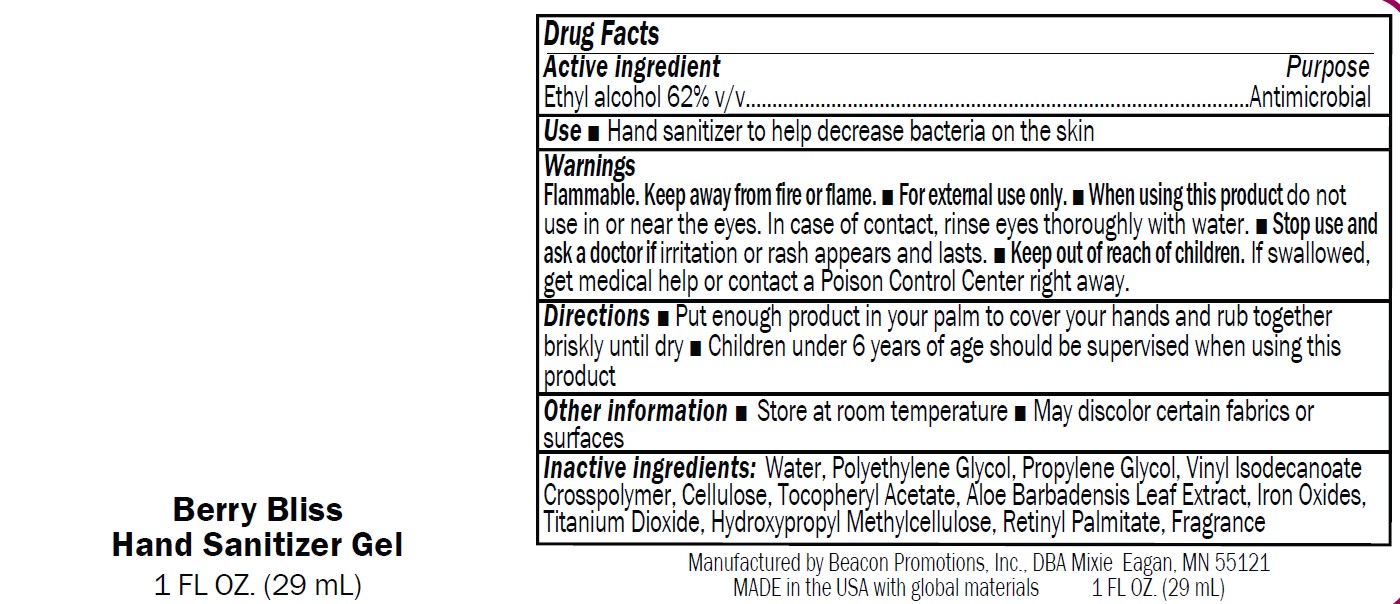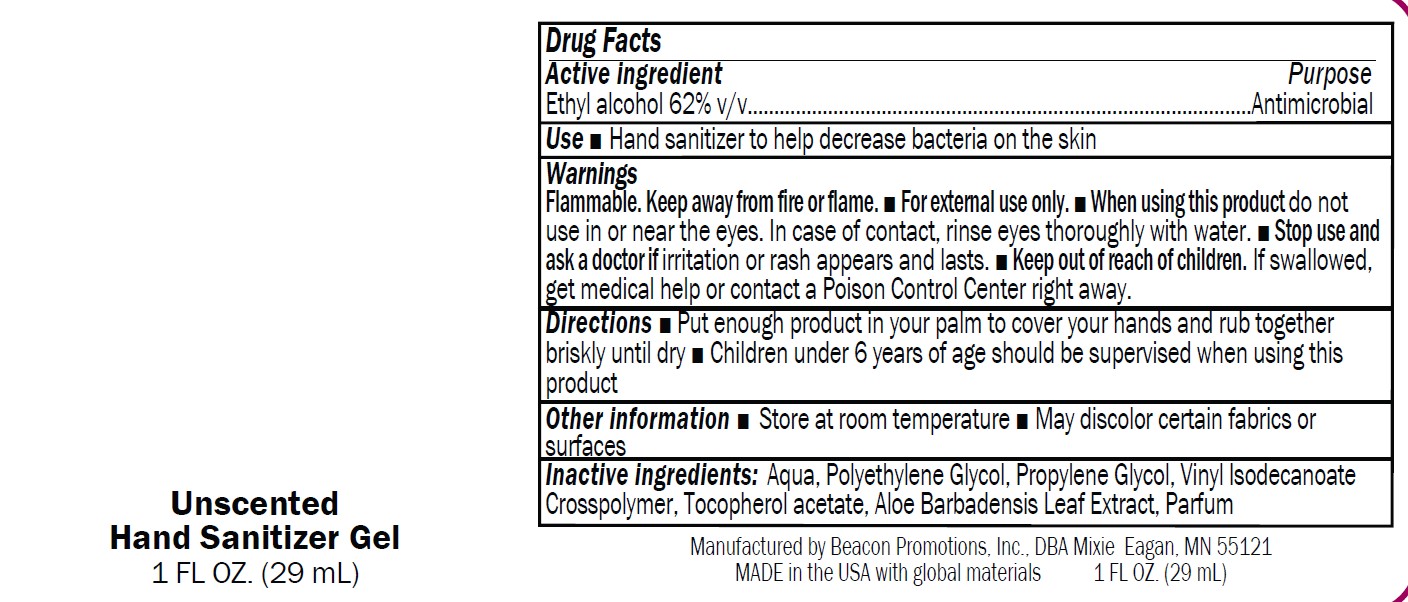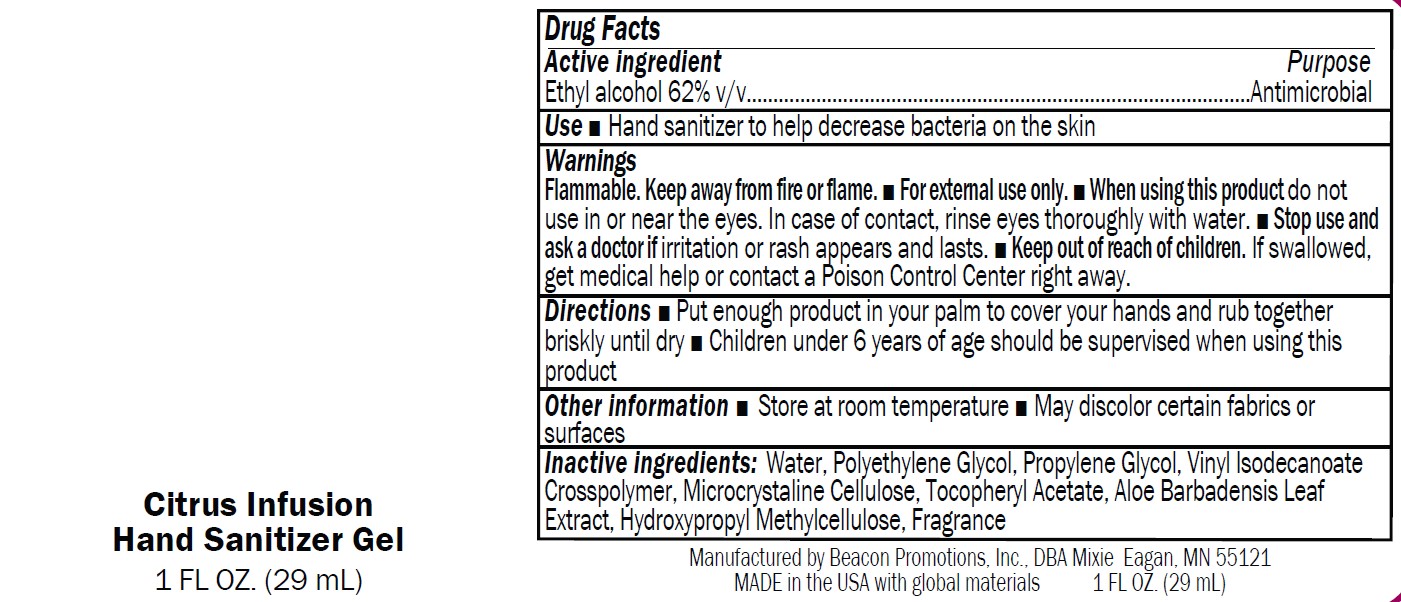 DRUG LABEL: SANMO-WH
NDC: 70445-601 | Form: GEL
Manufacturer: Beacon Promotions, Inc.
Category: otc | Type: HUMAN OTC DRUG LABEL
Date: 20240103

ACTIVE INGREDIENTS: ALCOHOL 63 mL/100 mL
INACTIVE INGREDIENTS: ACRYLATES/VINYL ISODECANOATE CROSSPOLYMER (10000 MPA.S NEUTRALIZED AT 0.5%); WATER; PROPYLENE GLYCOL; POLYETHYLENE GLYCOL 1000; ALOE; HYPROMELLOSE, UNSPECIFIED; MICROCRYSTALLINE CELLULOSE 101; .ALPHA.-TOCOPHEROL ACETATE

Antibacterial Gel

Drug facts

Ethyl alcohol 62%

Put enough product in your palm to cover your hands and rub together
briskly until dry

Purpose

Antimicrobial

USE

Hand sanitizer to help decrease bacteria on the skin

Warnings

Flammable. Keep away from fire or flame.

■ For external use only.

■ When using this product do not
use in or near the eyes. In case of contact, rinse eyes thoroughly with water.

■ Stop use and
ask a doctor if irritation or rash appears and lasts.

■ Keep out of reach of children.

If swallowed,get medical help or contact a Poison Control Center right away

Keep out of reach of children

Directions

■ Put enough product in your palm to cover your hands and rub together
briskly until dry

■ Children under 6 years of age should be supervised when using this
product

Drug Facts

Ethyl alcohol 62% v/v

Inactive Ingredients

Water, Polyethylene Glycol, Propylene Glycol, Vinyl Isodecanoate
Crosspolymer, Lactose, Cellulose, Tocopheryl Acetate, Aloe Barbadensis Leaf Extract,
Kaolin, Ultramarines, Hydroxypropyl Methylcellulose, Retinyl Palmitate, Fragrance

Other

■ Store at room temperature

■ May discolor certain fabrics or surfaces